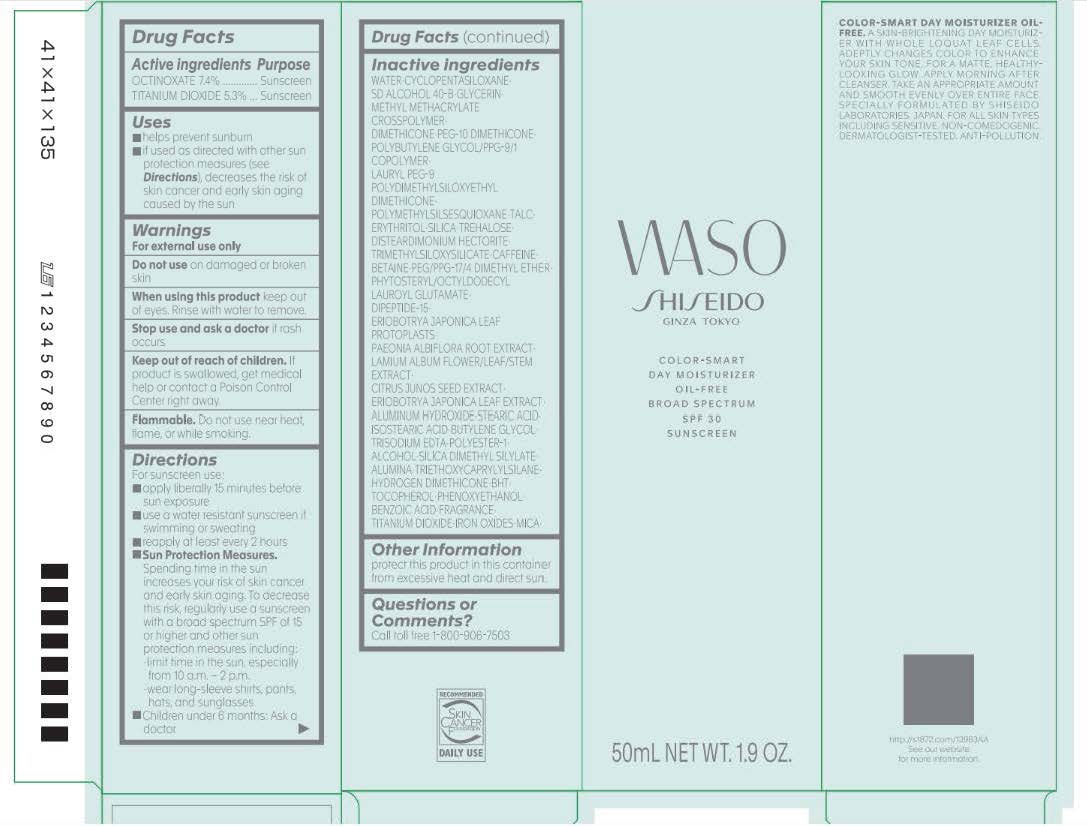 DRUG LABEL: SHISEIDO WASO COLOR-SMART DAY MOISTURIZER
NDC: 58411-966 | Form: CREAM
Manufacturer: Shiseido Americas Corporation
Category: otc | Type: HUMAN OTC DRUG LABEL
Date: 20260206

ACTIVE INGREDIENTS: OCTINOXATE 4.255 g/50 mL; TITANIUM DIOXIDE 3.0475 g/50 mL
INACTIVE INGREDIENTS: WATER; CYCLOPENTASILOXANE; DIMETHICONE; PEG-10 DIMETHICONE (600 CST); POLYMETHYLSILSESQUIOXANE (4.5 MICRONS); LAURYL PEG-9 POLYDIMETHYLSILOXYETHYL DIMETHICONE; TALC; ERYTHRITOL; SILICA; TREHALOSE; DISTEARDIMONIUM HECTORITE; BETAINE; CAFFEINE; PEG/PPG-17/4 DIMETHYL ETHER; PHYTOSTERYL/OCTYLDODECYL LAUROYL GLUTAMATE; DIPEPTIDE-15; PAEONIA LACTIFLORA ROOT; LAMIUM ALBUM FLOWERING TOP; CITRUS JUNOS SEED; ERIOBOTRYA JAPONICA LEAF; ALUMINUM HYDROXIDE; STEARIC ACID; ISOSTEARIC ACID; BUTYLENE GLYCOL; TRISODIUM EDTA; ALCOHOL; SILICA DIMETHYL SILYLATE; ALUMINA; TRIETHOXYCAPRYLYLSILANE; HYDROGEN DIMETHICONE (13 CST); BHT; TOCOPHEROL; PHENOXYETHANOL; BENZOIC ACID; FERRIC OXIDE RED; MICA; TRIMETHYLSILOXYSILICATE (M/Q 0.6-0.8)

SHISEIDO WASO COLOR-SMART DAY MOISTURIZER

Drug Facts

Active Ingredients | Purpose
OCTINOXATE 7.4% | Sunscreen
TITANIUM DIOXIDE 5.3% | Sunscreen

Uses

- helps prevent sunburn
- if used as directed with other sun protection measures (see Directions), decreases the risk of skin cancer and early skin aging caused by the sun

Warnings

For external use only

Do not useon damaged or broken skin

WHEN USING

When using this productkeep out of eyes. Rinse with water to remove.

Stop use and ask a doctorif rash occurs

Keep out of reach of children. If product is swallowed, get medical help or contact a Poison Control Center right away.

DO NOT USE

Flammable. Do not use near heat, flame, or while smoking

Directions

- apply liberally 15 minutes before sun exposure
- use a water resistant sun screen if swimming or sweating
- reapply at least every 2 hours
- Sun Protection Measures. Spending time in the sun increases your risk of skin cancer and early skin aging. To decrease this risk, regularly use a sunscreen with a broad spectrum SPF of 15 or higher and other sun protection measures including:

-limit time in the sun, especially from 10 a.m. - 2p.m.
-wear long-sleeve shirts, pant, hats, and sunglasses

- children under 6 months: Ask a doctor

Inactive Ingredients

WATER･CYCLOPENTASILOXANE･SD ALCOHOL 40-B･GLYCERIN･METHYL METHACRYLATE CROSSPOLYMER･DIMETHICONE･PEG-10 DIMETHICONE･POLYBUTYLENE GLYCOL/PPG-9/1 COPOLYMER･LAURYL PEG-9 POLYDIMETHYLSILOXYETHYL DIMETHICONE･POLYMETHYLSILSESQUIOXANE･TALC･ERYTHRITOL･SILICA･TREHALOSE･DISTEARDIMONIUM HECTORITE･TRIMETHYLSILOXYSILICATE･CAFFEINE･BETAINE･PEG/PPG-17/4 DIMETHYL ETHER･PHYTOSTERYL/OCTYLDODECYL LAUROYL GLUTAMATE･DIPEPTIDE-15･ERIOBOTRYA JAPONICA LEAF PROTOPLASTS･PAEONIA ALBIFLORA ROOT EXTRACT･LAMIUM ALBUM FLOWER/LEAF/STEM EXTRACT･CITRUS JUNOS SEED EXTRACT･ERIOBOTRYA JAPONICA LEAF EXTRACT･ALUMINUM HYDROXIDE･STEARIC ACID･ISOSTEARIC ACID･BUTYLENE GLYCOL･TRISODIUM EDTA･POLYESTER-1･ALCOHOL･SILICA DIMETHYL SILYLATE･ALUMINA･TRIETHOXYCAPRYLYLSILANE･HYDROGEN DIMETHICONE･BHT･TOCOPHEROL･PHENOXYETHANOL･BENZOIC ACID･FRAGRANCE･TITANIUM DIOXIDE･IRON OXIDES･MICA･

Other Information

protect this product in this container from excessive heat and direct sun.

Questions or Comments?

Call toll free-1-800-906-7503

PRINCIPLE DISPLAY PANEL- 50 mL

WASO

SHISEIDO

GINZA TOKYO

COLOR-SMART

DAY MOISTURIZER

OIL- FREE

BROAD SPECTRUM

SPF-30

SUNSCREEN

50 mL NET WT.1.9 OZ